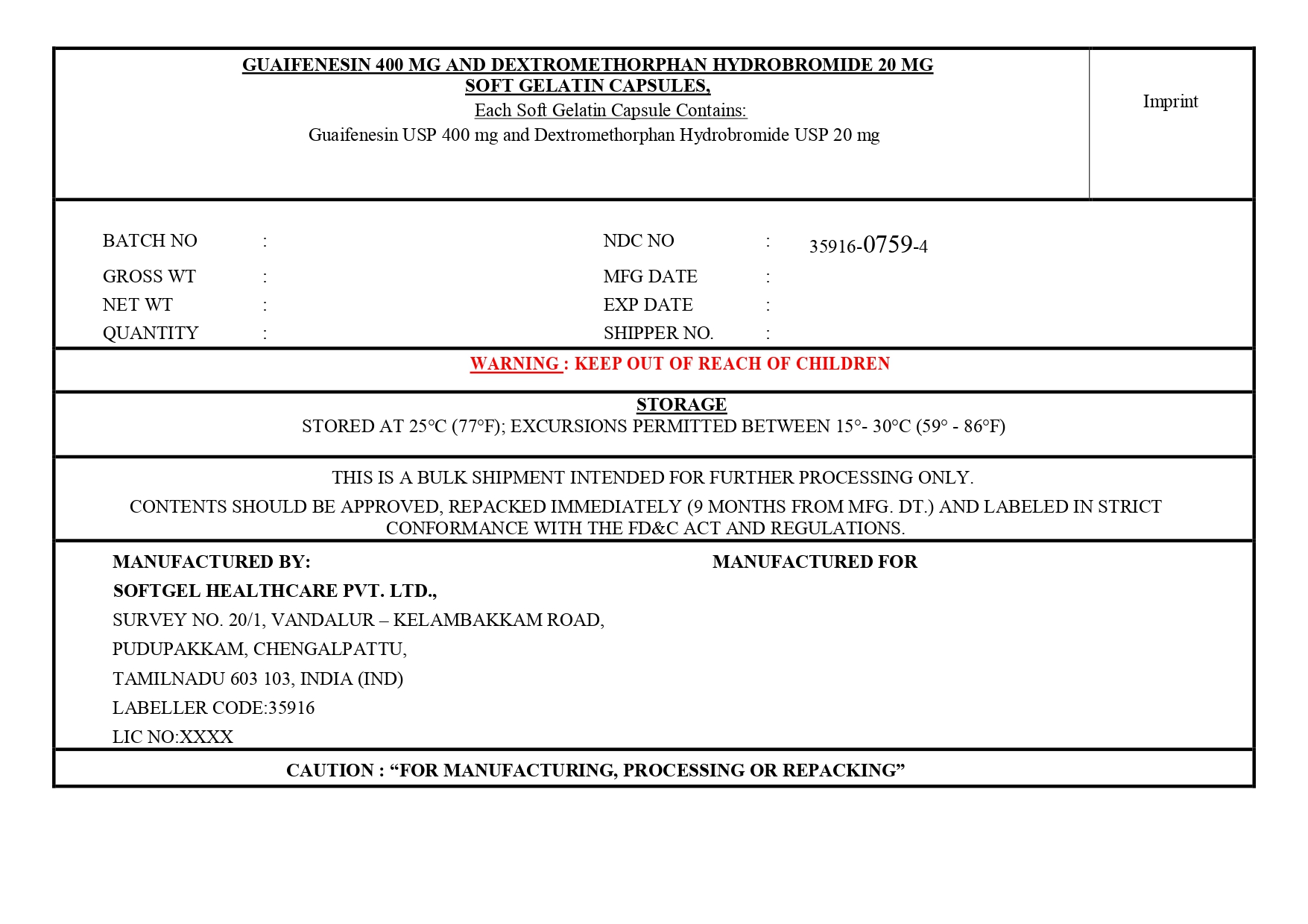 DRUG LABEL: Guaifenesin,Dextromethorphan Hbr
NDC: 35916-0759 | Form: CAPSULE, LIQUID FILLED
Manufacturer: Softgel Healthcare Pvt Ltd
Category: otc | Type: HUMAN OTC DRUG LABEL
Date: 20260114

ACTIVE INGREDIENTS: GUAIFENESIN 400 mg/1 1; DEXTROMETHORPHAN HYDROBROMIDE 20 mg/1 1
INACTIVE INGREDIENTS: GLYCERIN; WATER; POLYETHYLENE GLYCOL 400; GELATIN; POVIDONE K30; SORBITOL; PROPYLENE GLYCOL

Guaifenesin 400 mg and Dextromethorphan Hydrobromide 20 mg Softgelatin Capsules

Active ingredient (in each soft gelatin capsule)

Guaifenesin USP 400mg

Dextromethorphan HBr USP 20mg

Purposes

Expectorant

Cough suppressant

Uses

- temporarily relieves cough due to minor throat and bronchial irritation as may occur with a cold
- helps loosen phlegm (mucus) and thin bronchial secretions to rid the bronchial passageways of bothersome mucus and make coughs more productive

Warnings

Do not use

- if you are now taking a prescription monoamine oxidase inhibitor (MAOI) (certain drugs for depression, psychiatric, or emotional conditions, or Parkinson's disease), or for 2 weeks after stopping the MAOI drug. If you do not know if your prescription drug contains an MAOI, ask a doctor or pharmacist before taking this product.

Ask a doctor before use if you have

- cough accompained by excessive phlegm(mucus)
- persistent or chronic cough such as occurs with smoking,asthma,chronic bronchitis or emphysema

When using this product

- do not exceed recommended dosage
- do not use for more than 7 days

Stop use and ask a doctor if

- cough lasts for more than 7 days,recurs, or is accompanied by fever, rash, or persistent headache .

These could be signs of a serious condition.

PREGNANCY OR BREAST FEEDING

If pregnant or breast-feeding, ask a health professional before use.

Keep out of reach of children In case of accidental overdose, get medical help or contact a Poison Control Center right away.

Directions

- do not exceed 6 doses in 24 hours
- take with a full glass of water
- adults and children 12 years of age and over: take 1 softgel every 4 hours
- children under 12 years of age: do not use

Other information

- store at 25°C (77°F); excursions permitted between 15° -30°C (59° -86°F)
- Keep in dry place and do not expose to heat

Inactive ingredients

gelatin, glycerin, polyethylene glycol 400, povidone k-30,propylene glycol, purified water, sorbitol sorbitan solution